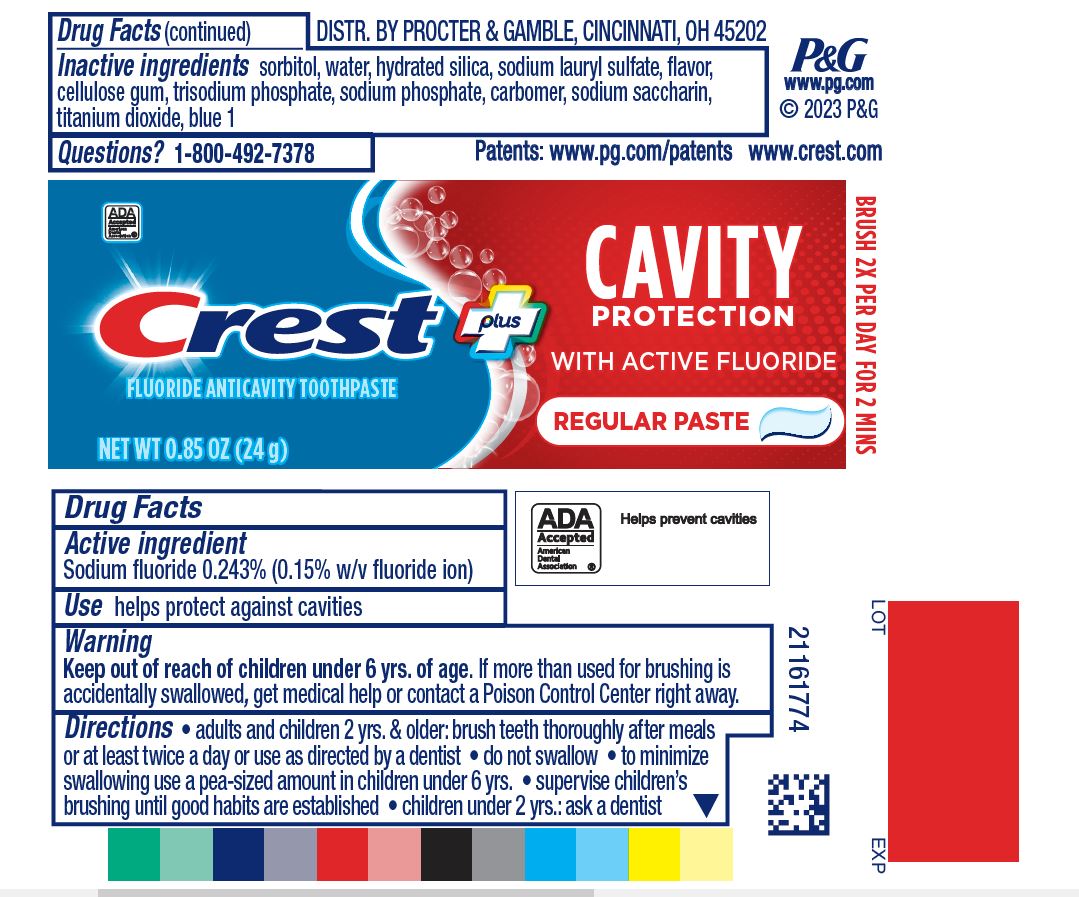 DRUG LABEL: Crest Cavity Protection
NDC: 69423-815 | Form: GEL, DENTIFRICE
Manufacturer: The Procter & Gamble Manufacturing Company
Category: otc | Type: HUMAN OTC DRUG LABEL
Date: 20260203

ACTIVE INGREDIENTS: SODIUM FLUORIDE 1.5 mg/1 g
INACTIVE INGREDIENTS: SACCHARIN SODIUM; SORBITOL; WATER; HYDRATED SILICA; SODIUM LAURYL SULFATE; SODIUM PHOSPHATE; FD&C BLUE NO. 1; CARBOXYMETHYLCELLULOSE SODIUM; SODIUM PHOSPHATE, TRIBASIC

Crest plus Cavity Protection Regular Paste

Drug Facts

Active ingredient

Sodium fluoride 0.243% (0.15% w/v fluoride ion)

Purpose

Anticavity toothpaste

Use

helps protect teeth and roots against cavities

Warnings

Keep out of reach of children under 6 yrs. of age.If more than used for brushing is accidentally swallowed, get medical help or contact a Poison Control Center right away.

Directions

- adults and children 2 yrs. & older: brush teeth thoroughly after meals or at least twice a day or use as directed by a dentist
  - do not swallow
  - to minimize swallowing use a pea-sized amount in children under 6
  - supervise children's brushing until good habits are established
- children under 2 yrs.: ask a dentist

Inactive ingredients

sorbitol, water, hydrated silica, sodium lauryl sulfate, trisodium phosphate, cellulose gum, flavor, sodium phosphate, sodium saccharin, carbomer, blue 1

Questions?

1-800-492-7378

Dist. by Procter & Gamble, Cincinnati OH 45202

www.crest.com

PRINCIPAL DISPLAY PANEL - 161 g Carton

Crest

Plus

FLUORIDE ANTICAVITY TOOTHPASTE

CAVITY PROTECTION WITH ACTIVE FLUORIDE

Regular Paste

Net Wt .85 OZ (24 g)